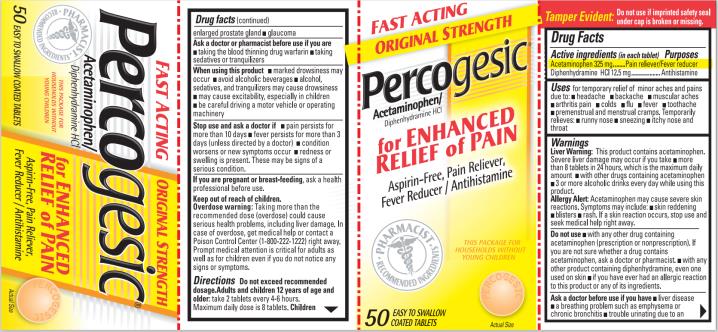 DRUG LABEL: Percogesic
NDC: 63029-053 | Form: TABLET, COATED
Manufacturer: Medtech Products Inc.
Category: otc | Type: HUMAN OTC DRUG LABEL
Date: 20250117

ACTIVE INGREDIENTS: ACETAMINOPHEN 325 mg/1 1; DIPHENHYDRAMINE HYDROCHLORIDE 12.5 mg/1 1
INACTIVE INGREDIENTS: CROSCARMELLOSE SODIUM; FD&C YELLOW NO. 6; HYPROMELLOSE, UNSPECIFIED; TALC; CELLULOSE, MICROCRYSTALLINE; LIGHT MINERAL OIL; POLYETHYLENE GLYCOL 400; SILICON DIOXIDE; STEARIC ACID; SODIUM STARCH GLYCOLATE TYPE A POTATO; STARCH, CORN; POVIDONE K30

Percogesic Original 63029-053

Drug Facts

Active Ingredients (in each tablet)

Acetaminophen 325 mg

Purpose

Pain reliever/fever reducer

Active Ingredients (in each tablet)

Diphenhydramine HCl 12.5 mg

Purpose

Antihistamine

Uses

for temporary relief of minor aches and pains due to:

- headache
- backache
- muscular aches
- arthritis pain
- colds
- flu
- fever
- toothache
- premenstrual and menstrual cramps

Temporarily relieves

- runny nose
- sneezing
- itchy nose and throat

Warnings

Liver Warning: This product contains acetaminophen. Severe liver damage may occur if you take

- more than 8 tablets in 24 hours, which is the maximum daily amount
- with other drugs containing acetaminophen
- 3 or more alcoholic drinks every day while using this product.

Allergy Alert: Acetaminophen may cause severe skin reactions. Symptoms may include:

- skin reddening
- blisters
- rash

If a skin reaction occurs, stop use and seek medical help right away.

Do not use

- with any other drug containing acetaminophen (prescription or nonprescription). If you are not sure whether a drug contains acetaminophen, ask a doctor or pharmacist.
- with any other product containing diphenhydramine, even one used on skin
- if you have ever had an allergic reaction to this product or any of its ingredients

Ask a doctor or pharmacist before use if you have

- liver disease
- a breathing problem such as emphysema or chronic bronchitis
- trouble urinating due to an enlarged prostate gland
- glaucoma

Ask a doctor or pharmacist before use if you are

- taking the blood thinning drug warfarin
- taking sedatives or tranquilizers

When using this product

- marked drowsiness may occur
- avoid alcoholic beverages
- alcohol, sedatives, and tranquilizers may cause drowsiness
- may cause excitability, especially in children
- be careful driving a motor vehicle or operating machinery

Stop use and ask a doctor if

- pain persists for more than 10 days
- fever persists for more than 3 days (unless directed by a doctor)
- condition worsens or new symptoms occur
- redness or swelling is present. These may be signs of a serious condition.

Overdose warning:

Taking more than the recommended dose (overdose) could cause serious health problems, including liver damage. In case of overdose, get medical help or contact a Poison Control Center (1-800-222-1222) right away. Prompt medical attention is critical for adults as well as for children even if you do not notice any signs or symptoms.

Directions

Do not exceed recommended dosage. Adults and children 12 years and older: take 2 tablets every 4-6 hours. Maximum daily dose is 8 tablets.

Children under 12 years of age: ask a doctor

Other Information

- store at controlled room temperature 15°-30°C (59°-86°F)
- avoid excessive heat

Inactive Ingredients

Croscarmellose Sodium, FD&C Yellow #6 Lake, Hypromellose, Magnesium Silicate, Magnesium Stearate, Microcrystalline Cellulose, Mineral Oil, Polyethylene Glycol, Polyvinylpyrrolidone, Pregelatinized Starch, Silica, Sodium Starch Glycolate and Stearic Acid

Questions?

1-800-443-4908

PRINCIPAL DISPLAY PANEL

ORIGINAL STRENGTH
Percogesic®
Acetaminophen/Diphenhydramine HCl
Aspirin-Free, Pain Reliever,
Fever Reducer/ Antihistamine
50 COATED TABLETS